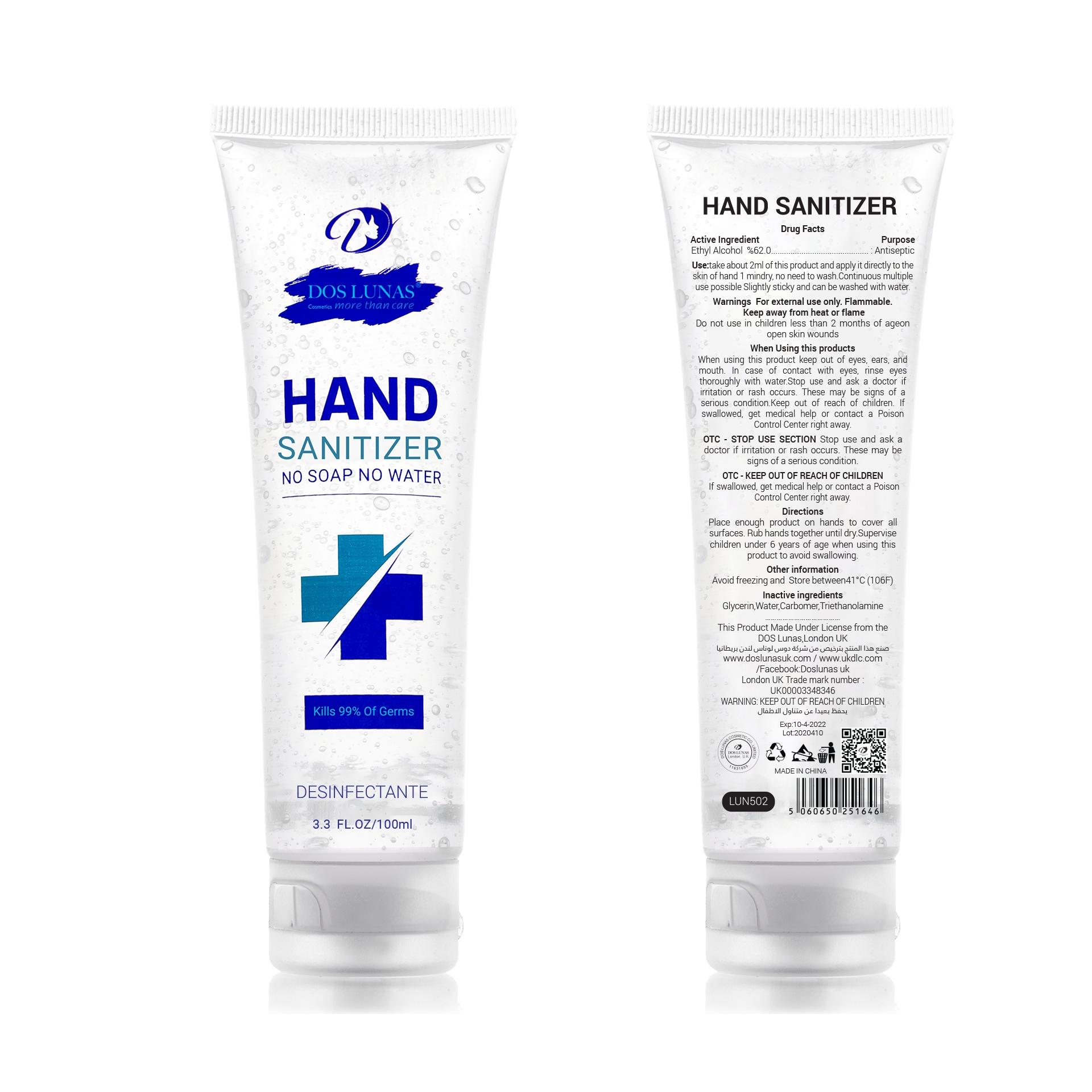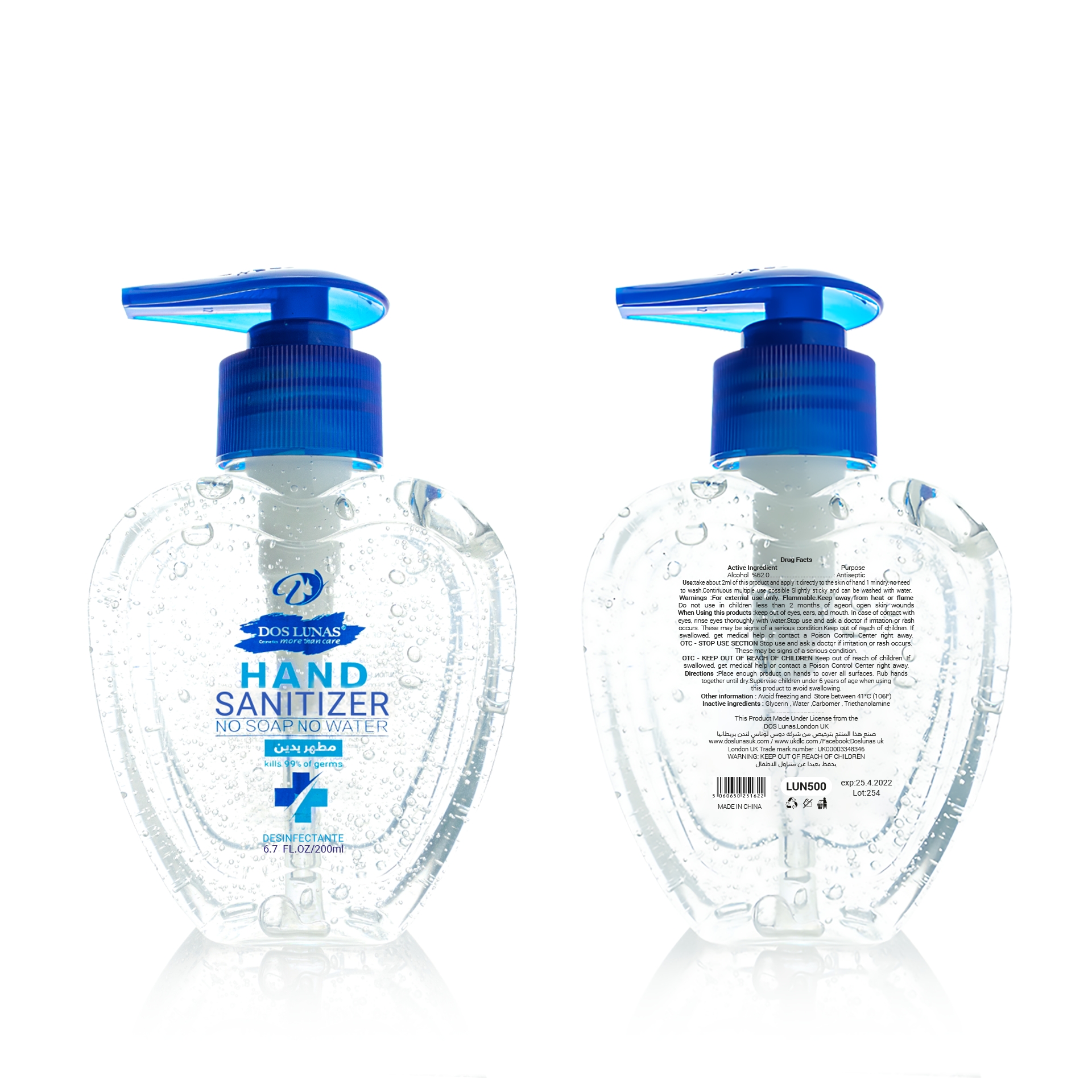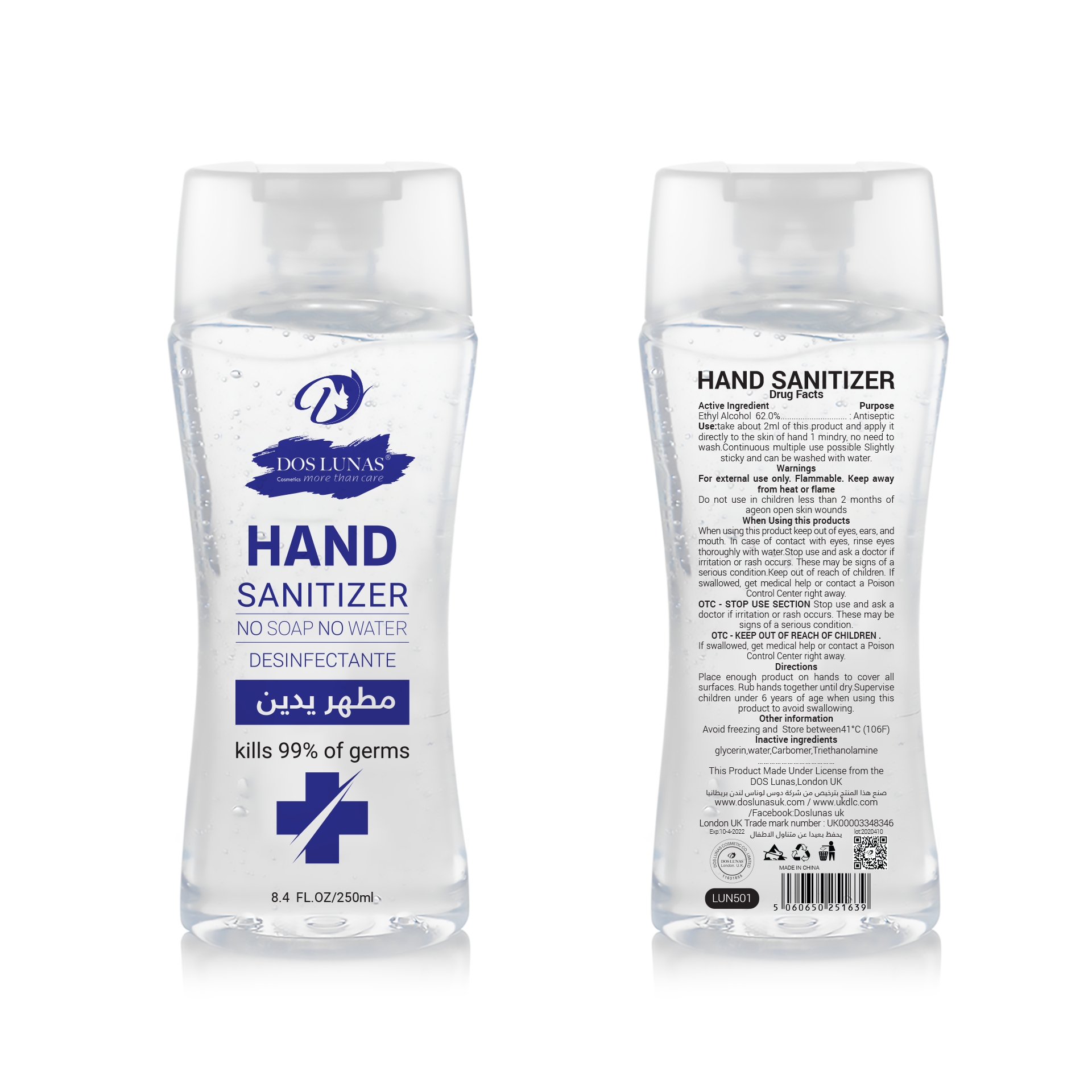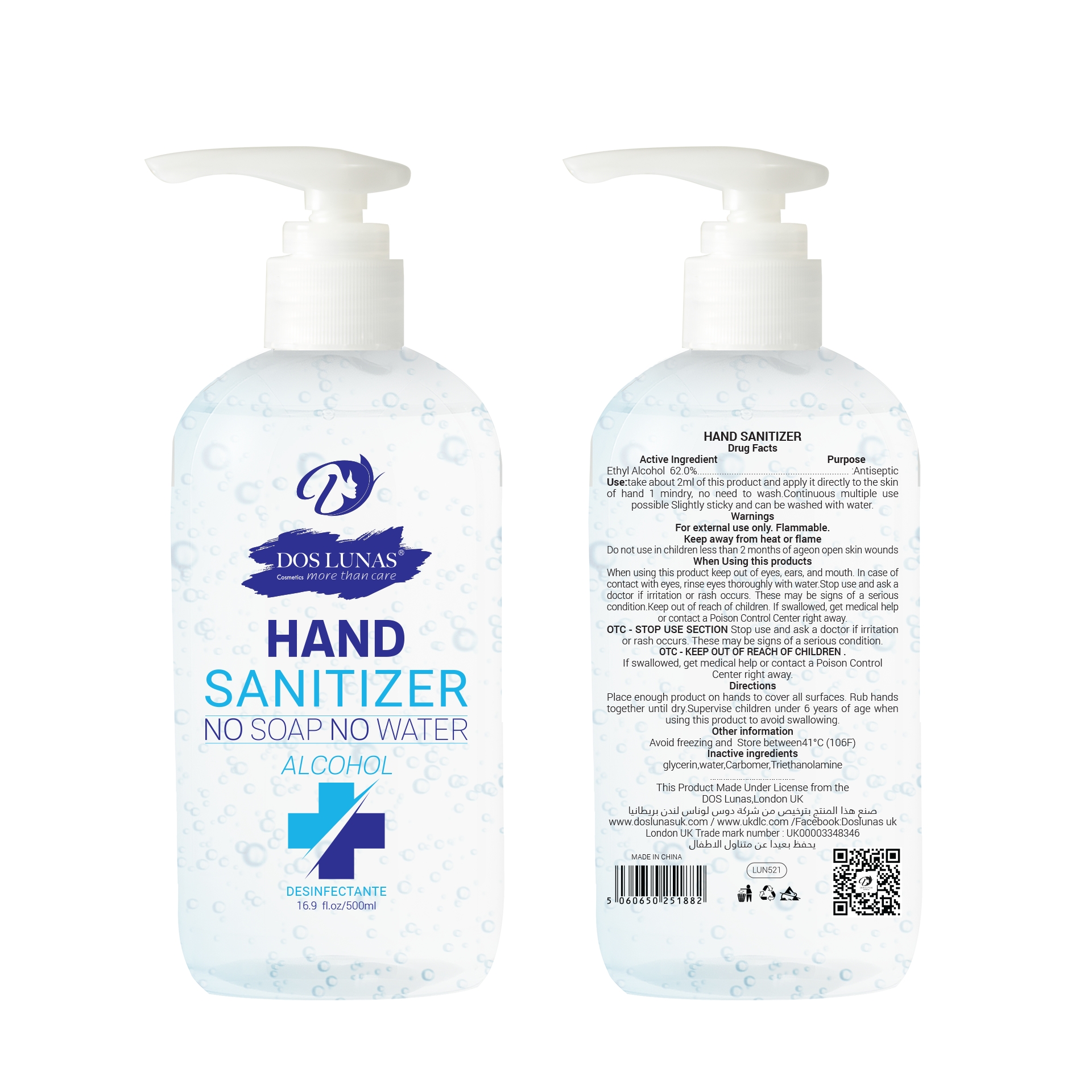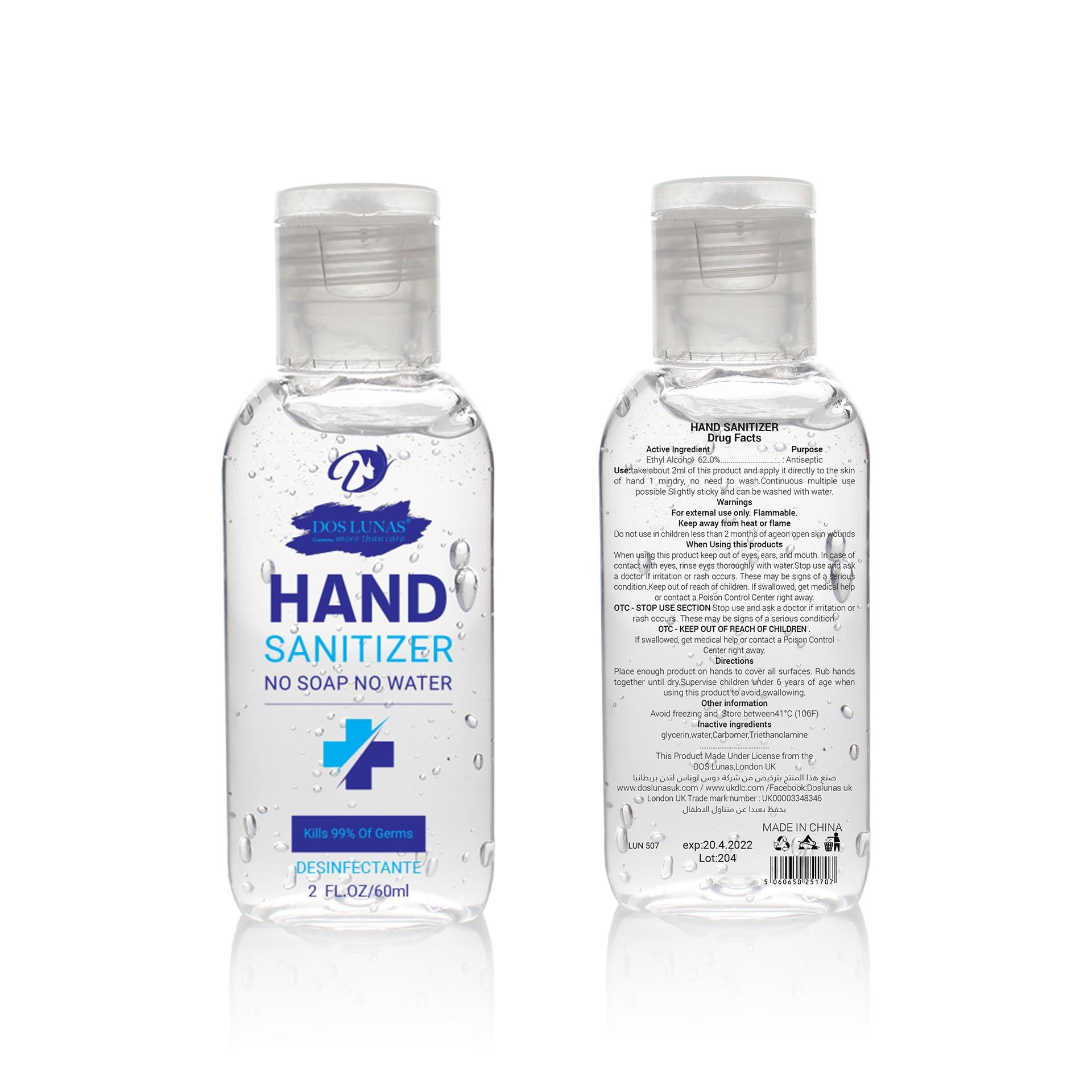 DRUG LABEL: Hand Sanitizer
NDC: 75759-001 | Form: GEL
Manufacturer: Yiwu Pafa Trading Firm (General Partnership)
Category: otc | Type: HUMAN OTC DRUG LABEL
Date: 20200508

ACTIVE INGREDIENTS: ALCOHOL 62 mL/100 mL
INACTIVE INGREDIENTS: GLYCERIN; CARBOMER HOMOPOLYMER TYPE C (ALLYL PENTAERYTHRITOL CROSSLINKED); WATER; TROLAMINE

Active Ingredient(s)

Ethyl Alcohol 62% v/v. Purpose: Antiseptic

Purpose

Antiseptic, Hand Sanitizer

Use

take about 2ml of this product and apply it directly to the skinof hand 1 mindy, no need to wash. Continuous multiple usepossible Slightly sticky and can be washed with water.

Warnings

For external use only. Flammable Keep away from heat or flame

Do not use

/

When using this product keep out of eyes, ears, and mouth. in case of contact with eyes, rinse eyes thoroughly with water Stop use and ask a doctor if irritation or rash occurs. These may be signs of a serious condition Keep out of reach of children. If swallowed, get medical helper contact a Poison Control Center right away

Stop use and ask a doctor if irritation or rash occurs. These may be signs of a serious condition.

KEEP OUT OF REACH OF CHILDREN

If swallowed, get medical help or contact a Poison Control Center right away

Directions

- Place enough product on hands to cover all surfaces. Rub hands together until dry Supervise children under 6 years of age when using this product to avoid swallowing

Other information

- Other information Avoid freezing and Store between41c(106F

Inactive ingredients

glycerin, water, Carbomer, Triethanolamine